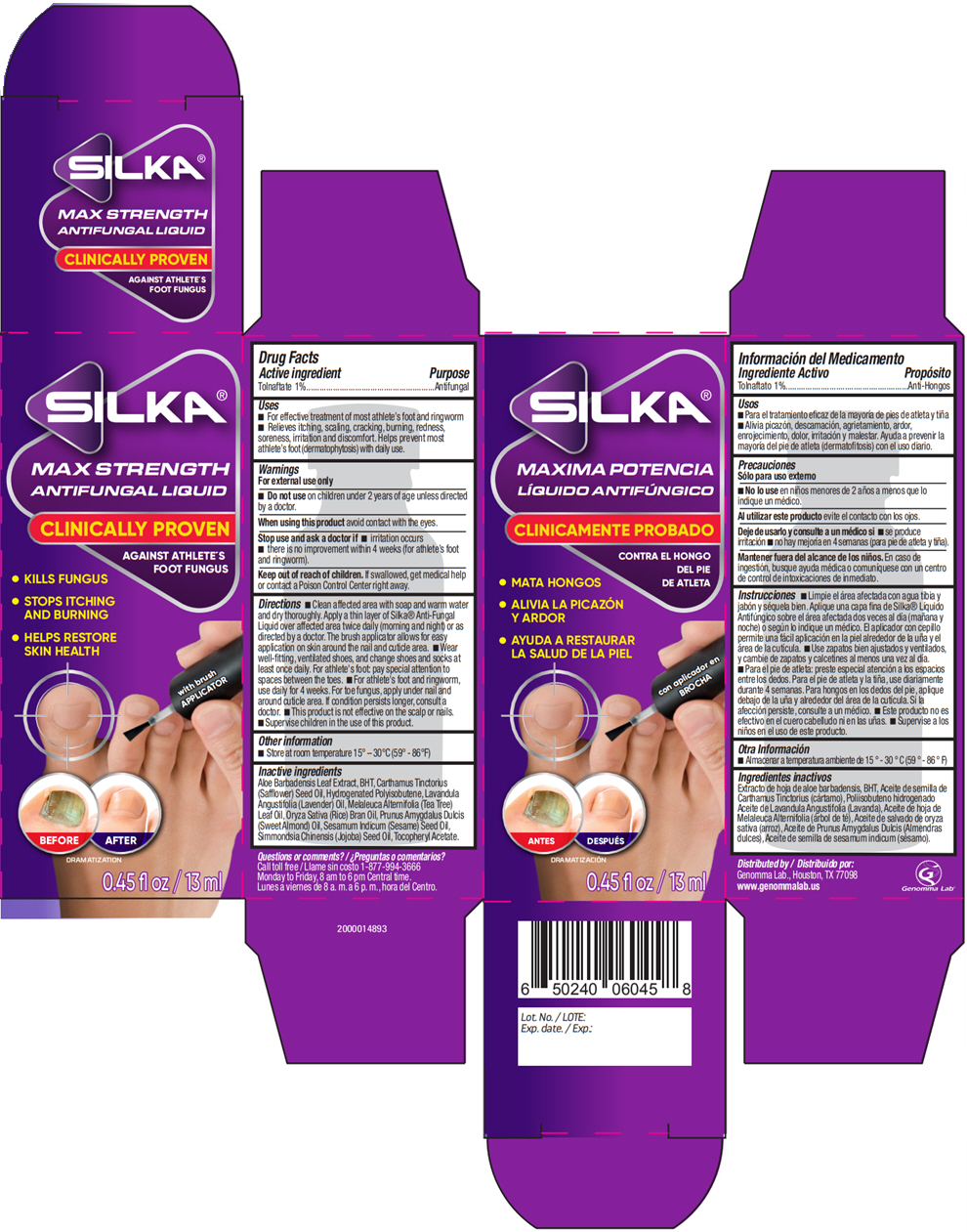 DRUG LABEL: Silka Antifungal
NDC: 50066-085 | Form: LIQUID
Manufacturer: Genomma Lab USA
Category: otc | Type: HUMAN OTC DRUG LABEL
Date: 20250930

ACTIVE INGREDIENTS: Tolnaftate 1 g/100 mL
INACTIVE INGREDIENTS: ALOE VERA LEAF; SAFFLOWER OIL; HYDROGENATED POLYISOBUTENE (1300 MW); LAVENDER OIL; TEA TREE OIL; RICE BRAN OIL; SESAME OIL

Silka® Liquid Antifungal

Drug Facts

Active ingredient

Tolnaftate 1%

Purpose

Antifungal

Uses

- For effective treatment of most athlete's foot and ringworm
- Relieves itching, scaling, cracking, burning, redness, soreness, irritation and discomfort. Helps prevent most athlete's foot (dermatophytosis) with daily use.

Warnings

For external use only

- Do not use on children under 2 years of age unless directed by a doctor.

When using this product avoid contact with the eyes.

Stop use and ask a doctor if

- irritation occurs
- there is no improvement within 4 weeks (for athlete's foot and ringworm).

Keep out of reach of children. If swallowed, get medical help or contact a Poison Control Center right away.

Directions

- Clean affected area with soap and warm water and dry thoroughly. Apply a thin layer of Silka® Anti-Fungal Liquid over affected area twice daily (morning and night) or as directed by a doctor. The brush applicator allows for easy application on skin around the nail and cuticle area.
- Wear well-ﬁtting, ventilated shoes, and change shoes and socks at least once daily. For athlete's foot: pay special attention to spaces between the toes.
- For athlete's foot and ringworm, use daily for 4 weeks. For toe fungus, apply under nail and around cuticle area. If condition persists longer, consult a doctor.
- This product is not effective on the scalp or nails.
- Supervise children in the use of this product.

Other information

- Store at room temperature 15° – 30°C (59° - 86°F)

Inactive ingredients

Aloe Barbadensis Leaf Extract, BHT, Carthamus Tinctorius (Safﬂower) Seed Oil, Hydrogenated Polyisobutene, Lavandula Angustifolia (Lavender) Oil, Melaleuca Alternifolia (Tea Tree) Leaf Oil, Oryza Sativa (Rice) Bran Oil, Prunus Amygdalus Dulcis (Sweet Almond) Oil, Sesamum Indicum (Sesame) Seed Oil, Simmondsia Chinensis (Jojoba) Seed Oil, Tocopheryl Acetate.

Questions or comments?

Call toll free 1-877-994-3666
Monday to Friday, 8 am to 6 pm Central time.

Distributed by
Genomma Lab., Houston, TX 77098

PRINCIPAL DISPLAY PANEL - 13 ml Bottle Carton

SILKA®

MAX STRENGTH
ANTIFUNGAL LIQUID

CLINICALLY PROVEN

AGAINST ATHLETE'S
FOOT FUNGUS

- KILLS FUNGUS
- STOPS ITCHING
  AND BURNING
- HELPS RESTORE
  SKIN HEALTH

with brush
APPLICATOR

BEFORE
AFTER
DRAMATIZATION

0.45 fl oz / 13 ml